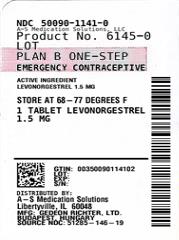 DRUG LABEL: Plan B One-Step
NDC: 50090-1141 | Form: TABLET
Manufacturer: A-S Medication Solutions
Category: otc | Type: HUMAN OTC DRUG LABEL
Date: 20210222

ACTIVE INGREDIENTS: LEVONORGESTREL 1.5 mg/1 1
INACTIVE INGREDIENTS: SILICON DIOXIDE; STARCH, POTATO; MAGNESIUM STEARATE; TALC; STARCH, CORN; LACTOSE MONOHYDRATE

Plan B One-Step®

Active ingredient

Levonorgestrel 1.5 mg

Purpose

Emergency contraceptive

Use

for women to reduce chance of pregnancy after unprotected sex (if a contraceptive failed or if you did not use birth control)

Warnings

Allergy alert: Do not use if you have ever had an allergic reaction to levonorgestrel.

Sexually transmitted diseases (STDs) alert: This product does not protect against HIV/AIDS or other STDs

Do not use

- if you are already pregnant (because it will not work)
- for regular birth control

Ask a doctor or pharmacist before use if you are taking efavirenz (HIV medication) or rifampin (tuberculosis treatment) or medication for seizures (epilepsy). These medications may reduce the effectiveness of levonorgestrel.

When using this product you may have

- menstrual changes
- nausea
- lower stomach (abdominal) pain
- tiredness
- headache
- dizziness
- breast pain
- vomiting

Keep out of reach of children.

In case of overdose, get medical help or contact a Poison Control center right away.

Directions

- take as soon as possible within 72 hours (3 days) after unprotected sex. The sooner you take it the better it will work.
- if you vomit within 2 hours after taking the medication, call a healthcare professional to find out if you should repeat the dose

Other information

- read the instructions, warnings and enclosed product leaflet before use
- this product works mainly by preventing ovulation (egg release). It may also prevent fertilization of a released egg (joining of sperm and egg) or attachment of a fertilized egg to the uterus (implantation).
- do not use if carton is open or tear strip is removed or blister seal is broken or missing.
- store at 20-25ºC (68-77ºF)

Inactive ingredients

colloidal silicon dioxide, corn starch, lactose monohydrate, magnesium stearate, potato starch, talc

Questions?

Call 1-800-330-1271 or visit www.PlanBOneStep.com

What is Plan B One-Step®?

Plan B One-Step® is emergency contraception that helps prevent pregnancy after birth control failure or unprotected sex. It is a backup method of preventing pregnancy and should not be used as regular birth control.

What Plan B One-Step® is not.

Plan B One-Step® will not work if you are already pregnant and will not affect an existing pregnancy. Plan B One-Step® will not protect you from HIV infection (the virus that causes AIDS) and other sexually transmitted diseases (STDs).

When should I use Plan B One-Step®?

The sooner you take emergency contraception, the better it works. You should use Plan B One-Step® within 72 hours (3 days) after you have had unprotected sex.

Plan B One-Step® is a backup or emergency method of birth control you can use when:

- your regular birth control was used incorrectly or failed
- you did not use any birth control method

When not to use Plan B One-Step®.

Plan B One-Step® should not be used:

- as a regular birth control method, because it’s not as effective as regular birth control.
- if you are already pregnant, because it will not work.
- if you are allergic to levonorgestrel or any other ingredients in Plan B One-Step®.

When should I talk to a doctor or pharmacist?

Ask a doctor or pharmacist before use if you are taking efavirenz (HIV medication) or rifampin (tuberculosis treatment) or medication for seizures (epilepsy). These medications may reduce the effectiveness of Plan B One-Step® and increase your chance of becoming pregnant. Your doctor may prescribe another form of emergency contraception that may not be affected by these medications.

How does Plan B One-Step® work?

Plan B One-Step® is one tablet with levonorgestrel, a hormone that has been used in many birth control pills for several decades. Plan B One-Step® contains a higher dose of levonorgestrel than birth control pills, but works in a similar way to prevent pregnancy. It works mainly by stopping the release of an egg from the ovary. It is possible that Plan B One-Step® may also work by preventing fertilization of an egg (the uniting of sperm with the egg) or by preventing attachment (implantation) to the uterus (womb).

How can I get the best results from Plan B One-Step®?

You have 72 hours (3 days) to try to prevent pregnancy after birth control failure or unprotected sex. The sooner you take Plan B One-Step®, the better it works.

How effective is Plan B One-Step®?

If Plan B One-Step® is taken as directed, it can significantly decrease the chance that you will get pregnant. About 7 out of every 8 women who would have gotten pregnant will not become pregnant.

How will I know Plan B One-Step® worked?

You will know Plan B One-Step® has been effective when you get your next period, which should come at the expected time, or within a week of the expected time. If your period is delayed beyond 1 week, it is possible you may be pregnant. You should get a pregnancy test and follow up with your healthcare professional.

Will I experience any side effects?

- some women may have changes in their period, such as a period that is heavier or lighter or a period that is early or late. If your period is more than a week late, you may be pregnant.
- if you have severe abdominal pain, you may have an ectopic pregnancy, and should get immediate medical attention.
- when used as directed, Plan B One-Step® is safe and effective. Side effects may include changes in your period, nausea, lower stomach (abdominal) pain, tiredness, headache, dizziness, and breast tenderness.
- if you vomit within 2 hours of taking the medication, call a healthcare professional to find out if you should repeat the dose.

What if I still have questions about Plan B One-Step®?

If you have questions or need more information, call our toll-free number, 1-800-330-1271, or visit our website at www.PlanBOneStep.com.

Keep out of reach of children:

In case of overdose, get medical help or contact a Poison Control Center right away at 1-800-222-1222.

Store at room temperature 20–25°C (68–77°F).

Active ingredient: levonorgestrel 1.5 mg

Inactive ingredients: colloidal silicon dioxide, potato starch, magnesium stearate, talc, corn starch, lactose monohydrate

1-800-330-1271 www.PlanBOneStep.com

If you are sexually active, you should see a healthcare provider for routine checkups. Your healthcare provider will talk to you about and, if necessary, test you for sexually transmitted diseases, teach you about effective methods of routine birth control, and answer any other questions you may have.

Manufacturer logo lock up PBOS logo lock up

©2017 Teva Women’s Health, Inc.

Rev. 7/2017 Printed in USA